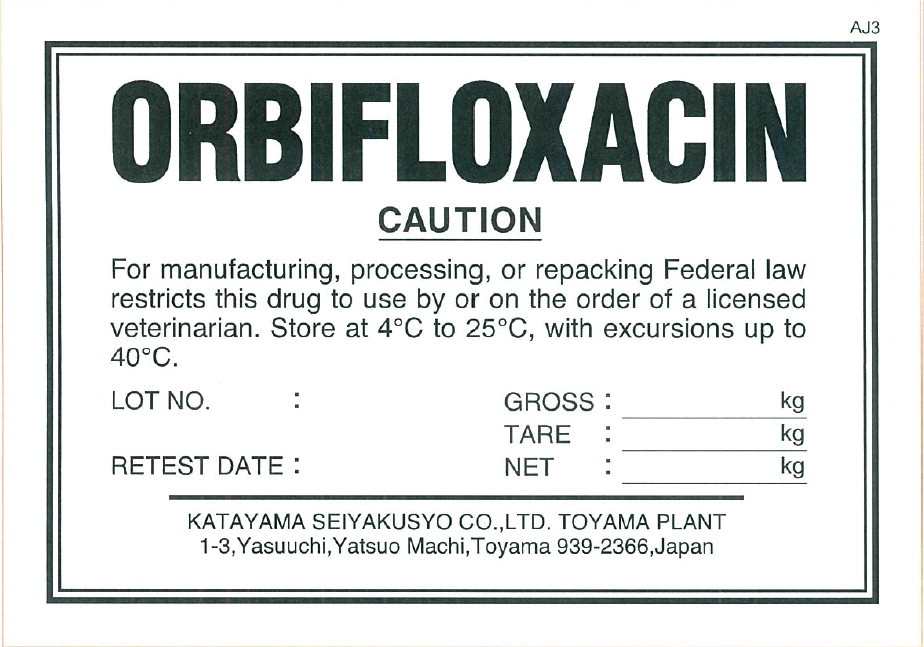 DRUG LABEL: Orbifloxacin
NDC: 42662-001 | Form: POWDER
Manufacturer: KATAYAMA SEIYAKUSYO CO., LTD.
Category: other | Type: BULK INGREDIENT - ANIMAL DRUG
Date: 20221219

ACTIVE INGREDIENTS: Orbifloxacin 1 kg/1 kg

Principal Display Panel – Drum Label

ORBIFLOXACIN

CAUTION

For manufacturing, processing, or repacking Federal law
restricts this drug to use by or on the order of a licensed
veterinarian. Store at 4°C to 25°C, with excursions up to
40°C.

LOT NO.: GROSS: kg

TARE: kg

RETESTED DATE: NET: kg

KATAYAMA SEIYAKUSYO CO., LTD. TOYAMA PLANT

1-3 Yasuuchi, Yatsuo Machi, Toyama 939-2366, Japan